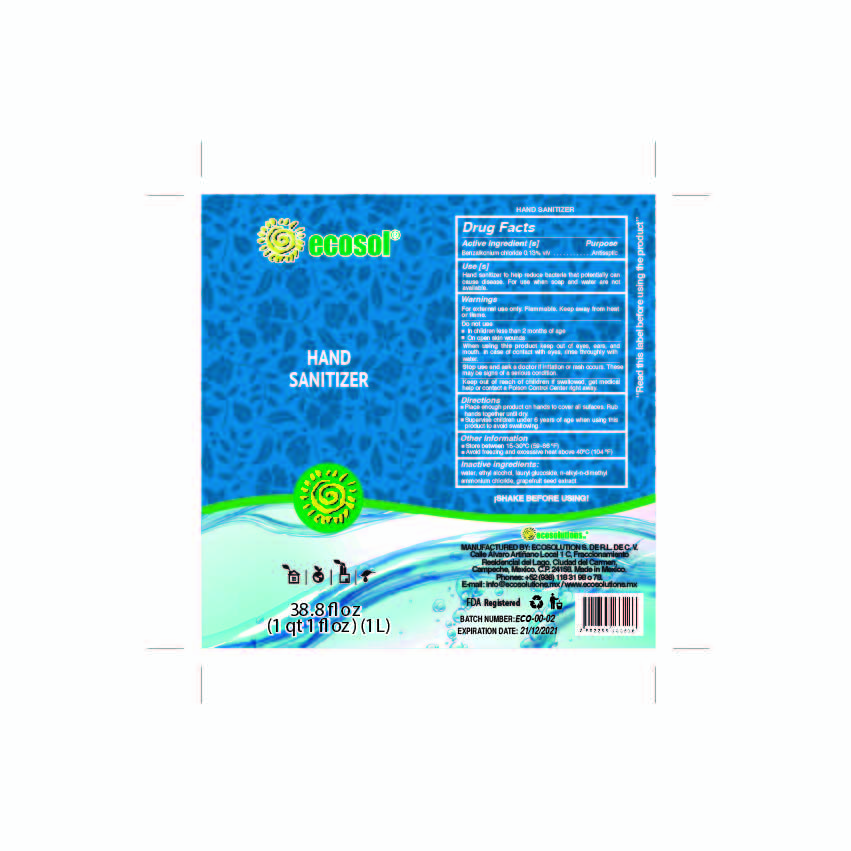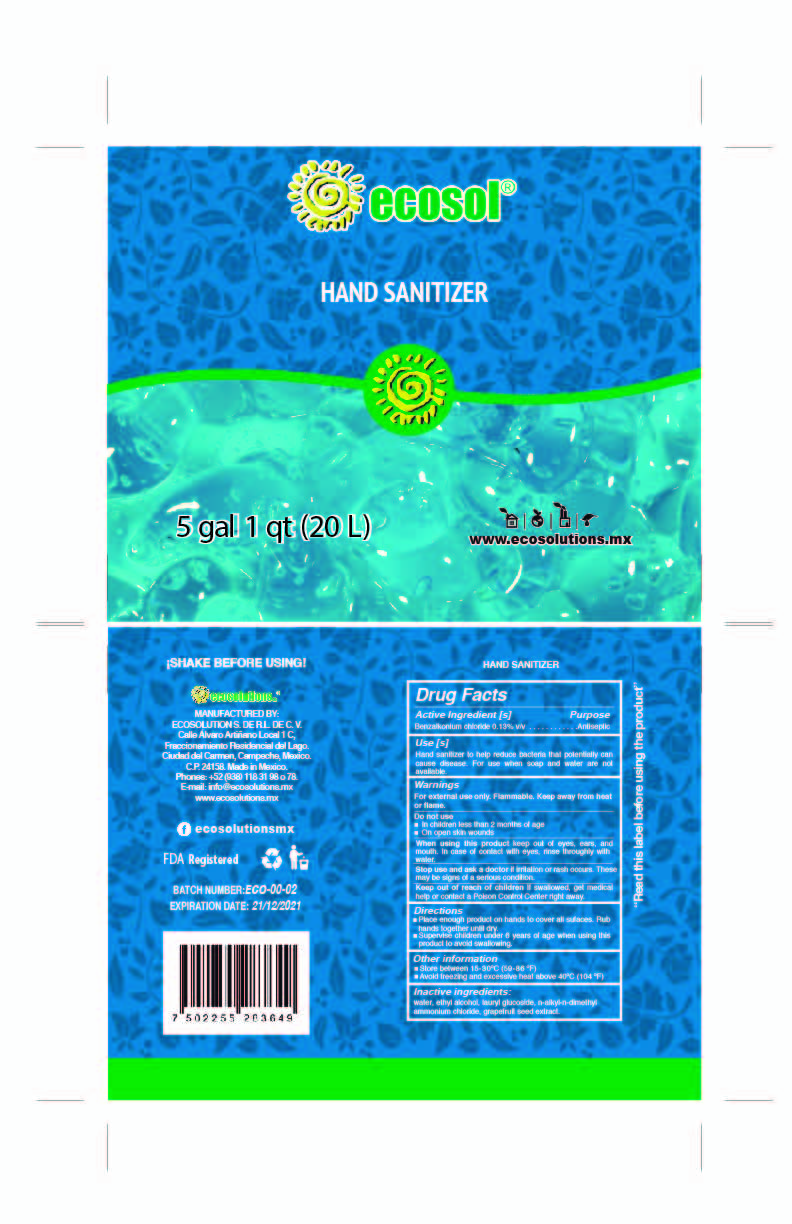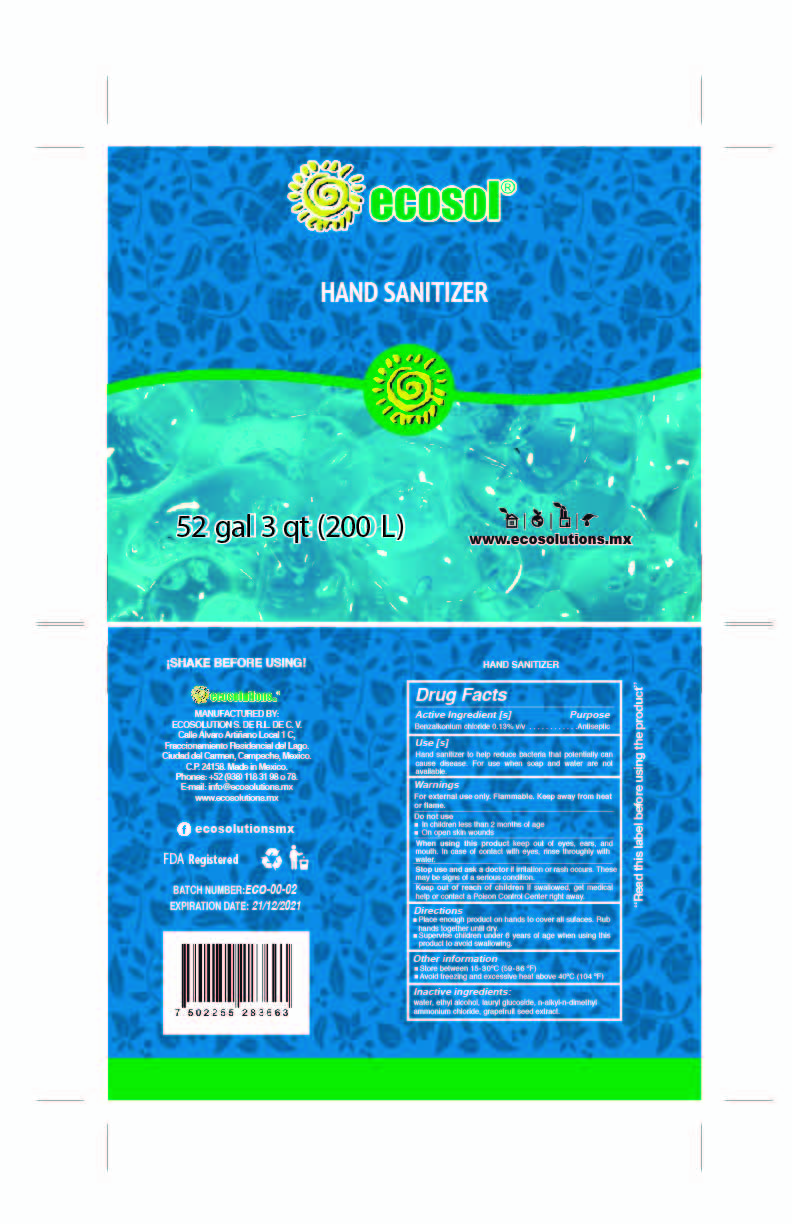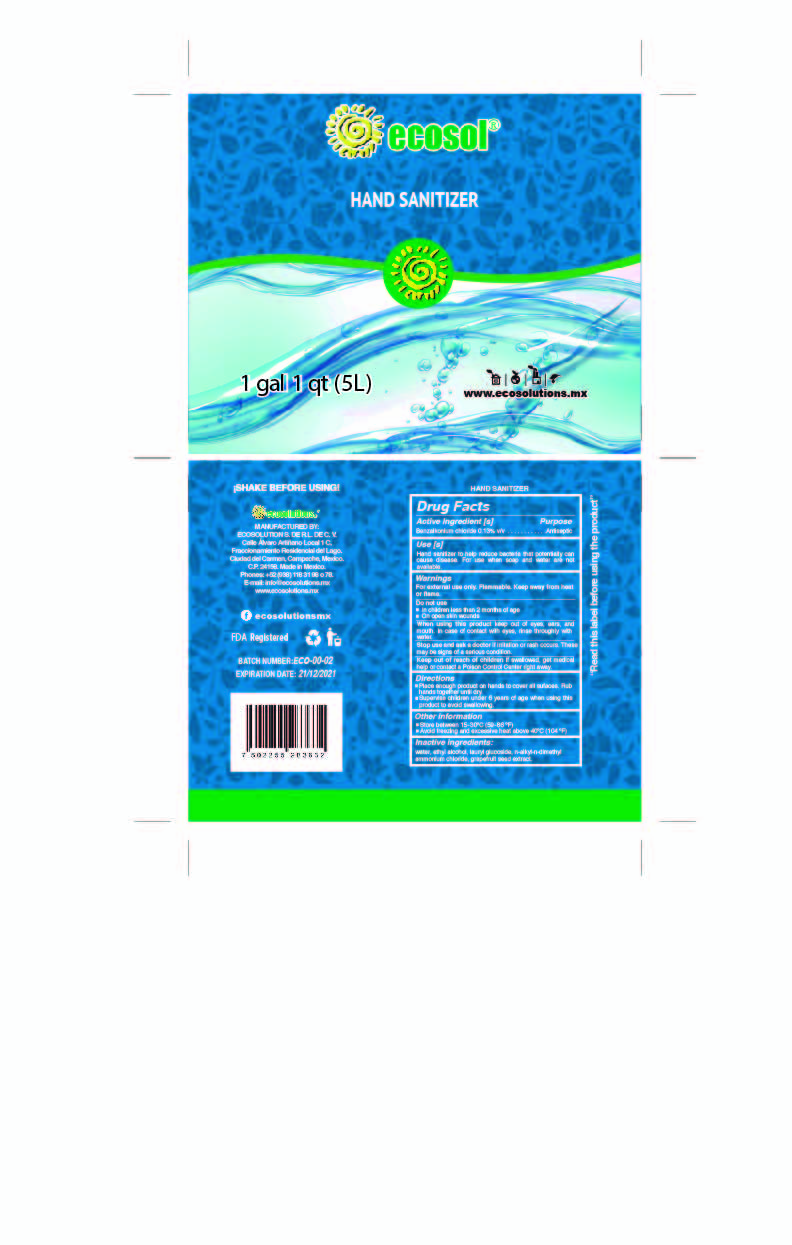 DRUG LABEL: Ecosol Hand sanitizer
NDC: 77993-005 | Form: LIQUID
Manufacturer: Ecosolutions, S. de R.L. de C.V.
Category: otc | Type: HUMAN OTC DRUG LABEL
Date: 20200921

ACTIVE INGREDIENTS: BENZALKONIUM CHLORIDE 0.13 g/100 mL
INACTIVE INGREDIENTS: 3-CHLORO-2-HYDROXYPROPYLCOCOALKYLDIMETHYLAMMONIUM CHLORIDE 0.03 mL/100 mL; LAURYL GLUCOSIDE 0.45 mL/100 mL; WATER 98.89 mL/100 mL; GRAPEFRUIT SEED OIL 0.03 mL/100 mL; METHYL ALCOHOL 0.47 mL/100 mL

Hand sanitizer

Active Ingredient(s)

Benzalkonium chloride 0.13% v/v. Purpose: Antiseptic

Purpose

Antiseptic, Hand Sanitizer

Use

Hand Sanitizer to help reduce bacteria that potentially can cause disease. For use when soap and water are not available.

Warnings

For external use only. Flammable. Keep away from heat or flame

Do not use

- in children less than 2 months of age
- on open skin wounds

When using this product keep out of eyes, ears, and mouth. In case of contact with eyes, rinse eyes thoroughly with water.
Stop use and ask a doctor if irritation or rash occurs. These may be signs of a serious condition.
Keep out of reach of children. If swallowed, get medical help or contact a Poison Control Center right away.

Stop use and ask a doctor if irritation or rash occurs. These may be signs of a serious condition.

Keep out of reach of children. If swallowed, get medical help or contact a Poison Control Center right away.

Directions

- Place enough product on hands to cover all surfaces. Rub hands together until dry.
- Supervise children under 6 years of age when using this product to avoid swallowing.

Other information

- Store between 15-30C (59-86F)
- Avoid freezing and excessive heat above 40C (104F)

Inactive ingredients

water, ethyl alcohol, lauryl glucoside, n-alkyl-n-dimethyl ammonium chloride, grapefruit seed extract.

PDP

1000 mL NDC: 77993-005-01

5000 mL NDC: 77993-005-02

20000 mL NDC: 77993-005-03

200000 mL NDC: 77993-005-04